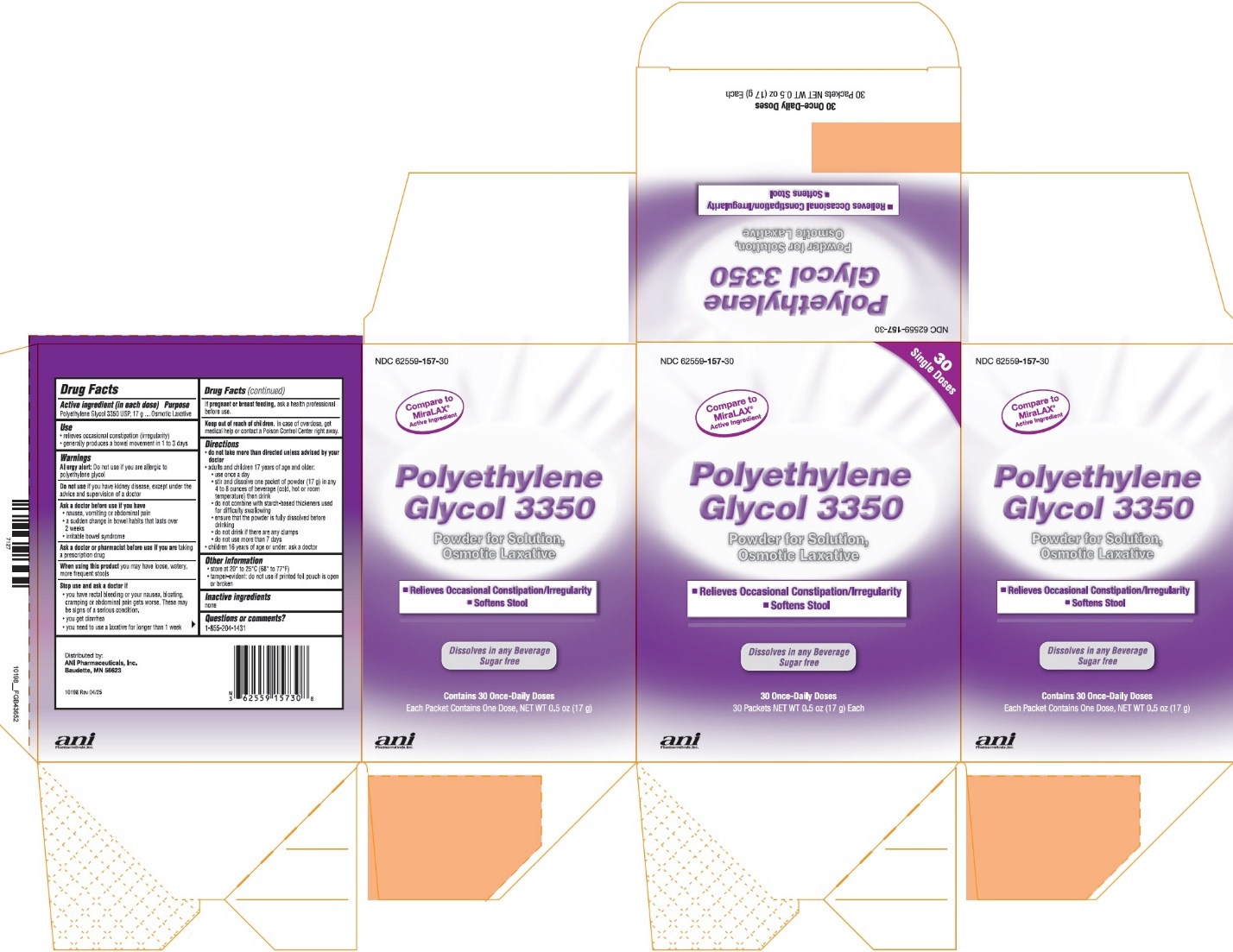 DRUG LABEL: Polyethylene Glycol 3350
NDC: 62559-157 | Form: POWDER, FOR SOLUTION
Manufacturer: ANI Pharmaceuticals, Inc.
Category: otc | Type: HUMAN OTC DRUG LABEL
Date: 20251210

ACTIVE INGREDIENTS: POLYETHYLENE GLYCOL 3350 17 g/17 g

Polyethylene Glycol 3350

Active Ingredient (in each dose)

Polyethylene Glycol 3350 USP, 17g

Purpose

Osmotic Laxative

Use

- relieves occasional constipation (irregularity)
- generally produces a bowel movement in 1 to 3 days

Warnings

Allergy alert:

Do not use if you are allergic to polyethylene glycol

Do not use

if you have kidney disease, except under the advice and supervision of a doctor

Ask a doctor before use if you have

- nausea, vomiting or abdominal pain
- a sudden change in bowel habits that lasts over 2 weeks
- irritable bowel syndrome

Ask a doctor or pharmacist before use if you are

taking a prescription drug

When using this product

you may have loose, watery, more frequent stools

Stop use and ask a doctor if

- you have rectal bleeding or your nausea, bloating, cramping or abdominal pain gets worse. These may be signs of a serious condition.
- you get diarrhea
- you need to use a laxative for longer than 1 week

If pregnant or breast feeding,

ask a health professional before use.

Keep out of reach of children.

In case of overdose, get medical help or contact a Poison Control Center right away.

Directions

- do not take more than directed unless advised by your doctor
- adults and children 17 years of age and older:
  - use once a day
  - stir and dissolve one packet of powder (17 g) in any 4 to 8 ounces of beverage (cold, hot or room temperature) then drink
  - do not combine with starch-based thickeners used for difficulty swallowing
  - ensure that the powder is fully dissolved before drinking
  - do not drink if there are any clumps
  - do not use more than 7 days
- children 16 years of age or under: ask a doctor

Other information

- store at 20° to 25°C (68° to 77°F)
- tamper-evident: do not use if printed foil pouch is open or broken

Inactive ingredients

None

Questions or comments?

1-855-204-1431

Distributed by:
ANI Pharmaceuticals, Inc.
Baudette, MN 56623

10198 Rev 04/25

PRINCIPAL DISPLAY PANEL

NDC 62559-157-30
Polyethylene Glycol 3350
Powder for Solution,
Osmotic Laxative

- Relieves Occasional Constipation/Irregularity
- Softens Stool

Dissolves in any Beverage
Sugar free

30 Once-Daily Doses
30 Packets NET WT 0.5 oz (17 g) Each
30 Single Doses
Compare to MiraLAX® Active Ingredient